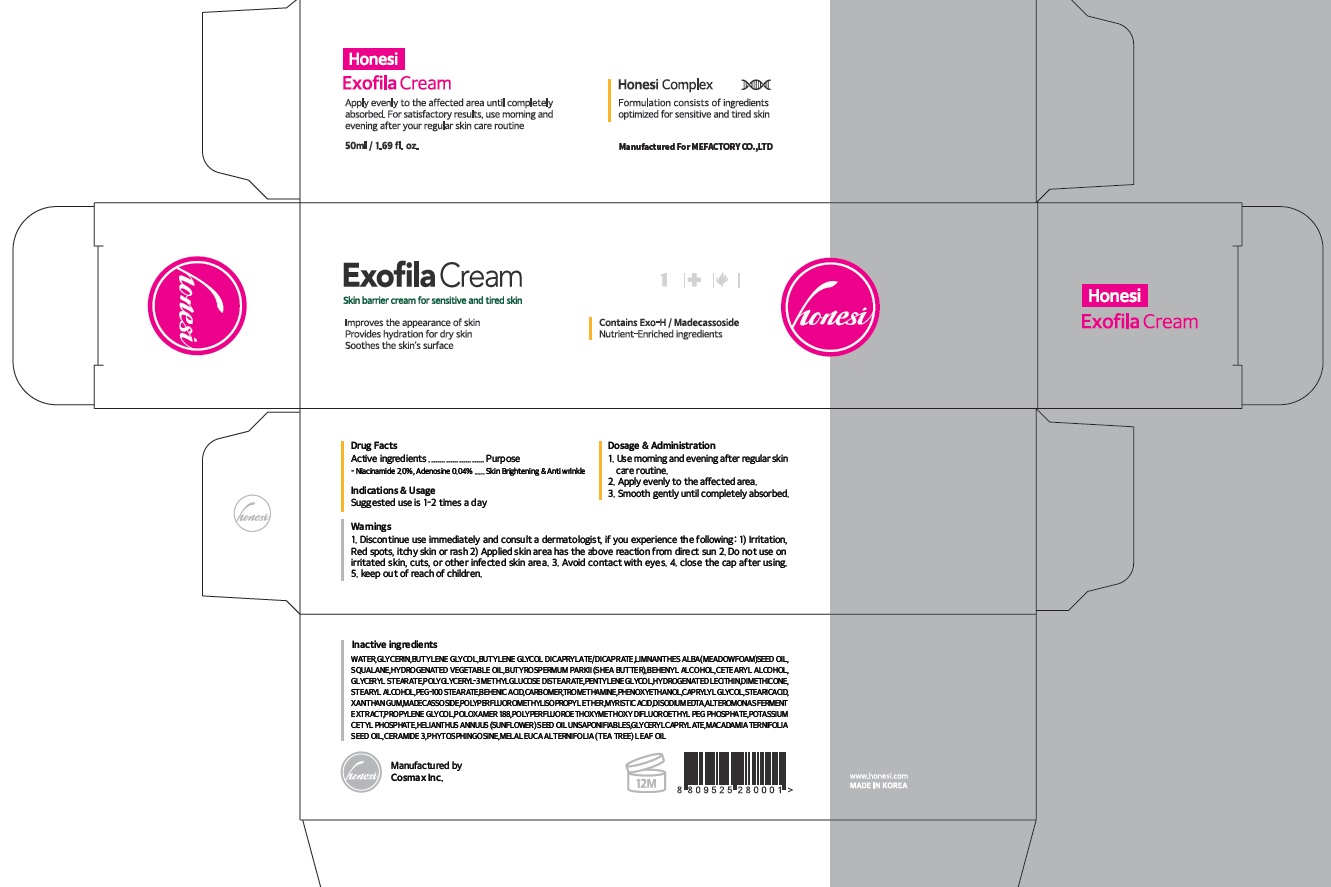 DRUG LABEL: Honesi exofila crea m
NDC: 70908-210 | Form: CREAM
Manufacturer: MeFactory Co., Ltd.
Category: otc | Type: HUMAN OTC DRUG LABEL
Date: 20180830

ACTIVE INGREDIENTS: Niacinamide 1.0 g/50 mL; Adenosine 0.02 g/50 mL
INACTIVE INGREDIENTS: WATER; GLYCERIN

ACTIVE INGREDIENT

Active ingredients: Niacinamide 2.0%, Adenosine 0.04%

INACTIVE INGREDIENT

Inactive ingredients: WATER,GLYCERIN,BUTYLENE GLYCOL,BUTYLENE GLYCOL DICAPRYLATE/DICAPRATE,LIMNANTHES ALBA (MEADOWFOAM) SEED OIL,SQUALANE,HYDROGENATED VEGETABLE OIL,BUTYROSPERMUM PARKII (SHEA BUTTER),BEHENYL ALCOHOL,CETEARYL ALCOHOL,GLYCERYL STEARATE,POLYGLYCERYL-3 METHYLGLUCOSE DISTEARATE,PENTYLENE GLYCOL,HYDROGENATED LECITHIN,DIMETHICONE,STEARYL ALCOHOL,PEG-100 STEARATE,BEHENIC ACID,CARBOMER,TROMETHAMINE,PHENOXYETHANOL,CAPRYLYL GLYCOL,STEARIC ACID,XANTHAN GUM,MADECASSOSIDE,POLYPERFLUOROMETHYLISOPROPYL ETHER,MYRISTIC ACID,DISODIUM EDTA,ALTEROMONAS FERMENT EXTRACT,PROPYLENE GLYCOL,POLOXAMER 188,POLYPERFLUOROETHOXYMETHOXY DIFLUOROETHYL PEG PHOSPHATE,POTASSIUM CETYL PHOSPHATE,HELIANTHUS ANNUUS (SUNFLOWER) SEED OIL UNSAPONIFIABLES,GLYCERYL CAPRYLATE,MACADAMIA TERNIFOLIA SEED OIL,CERAMIDE 3,PHYTOSPHINGOSINE,MELALEUCA ALTERNIFOLIA (TEA TREE) LEAF OIL

PURPOSE

Purpose: Skin Brightening & Anti wrinkle

WARNINGS

Warnings: 1. Discontinue use immediately and consult a dermatologist, if you experience the following: 1) Irritation, Red spots, itchy skin or rash 2) Applied skin area has the above reaction from direct sun 2. Do not use on irritated skin, cuts, or other infected skin area. 3. Avoid contact with eyes. 4. close the cap after using. 5. keep out of reach of children.

KEEP OUT OF REACH OF CHILDREN

INDICATIONS & USAGE

Indications & Usage: Suggested use is 1-2 times a day

DOSAGE & ADMINISTRATION

Dosage & Administration: 1. use morning and evening after regular skin care routine. 2. Apply evenly to the affected area. 3. smooth gently until completely absorbed.